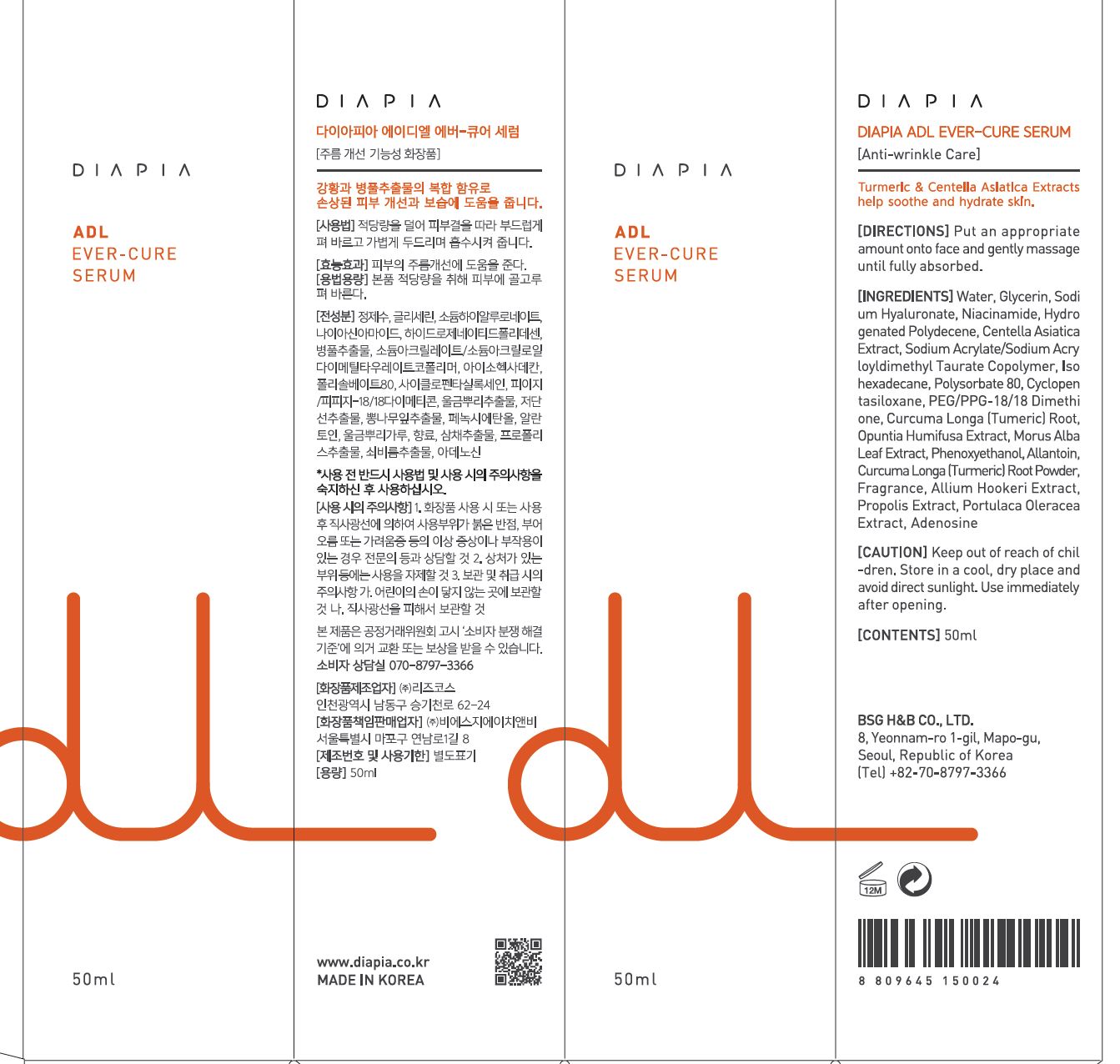 DRUG LABEL: DIAPIA ADL EVER-CURE SERUM
NDC: 71857-0011 | Form: LIQUID
Manufacturer: BSG H & B Co., Ltd.
Category: otc | Type: HUMAN OTC DRUG LABEL
Date: 20211201

ACTIVE INGREDIENTS: ADENOSINE 0.04 g/100 mL; NIACINAMIDE 2 g/100 mL
INACTIVE INGREDIENTS: WATER

Drug Facts

ACTIVE INGREDIENT

Niacinamide, Adenosine

INACTIVE INGREDIENT

Water, Glycerin, Sodium Hyaluronate, Hydrogenated Polydecene, Centella Asiatica Extract, Sodium Acrylate/Sodium Acryloyldimethyl Taurate Copolymer, Isohexadecane, Polysorbate 80, Cyclopentasiloxane, PEG/PPG-18/18 Dimethicone, Curcuma Longa (Tumeric) Root Extract, Opuntia Humifusa Extract, Morus Alba Leaf Extract, Phenoxyethanol, Allantoin, Curcuma Longa (Turmeric) Root Powder, Fragrance, Allium Hookeri Extract, Propolis Extract, Portulaca Oleracea Extract

PURPOSE

Brightening & Anti-wrinkle care, Soothing, Moisturizing, Relieving itching skin

keep out of reach of the children

INDICATIONS AND USAGE

Put the appropriate amount onto face and gently massage until fully absorbed.

WARNINGS

1.Keep out of reach of children.

2.Store in a cool, dry place and avoid direct sunlight.

3.If abnormal symptoms occur after use, stop use and consult with a skin specialist.

DOSAGE AND ADMINISTRATION

for external use only